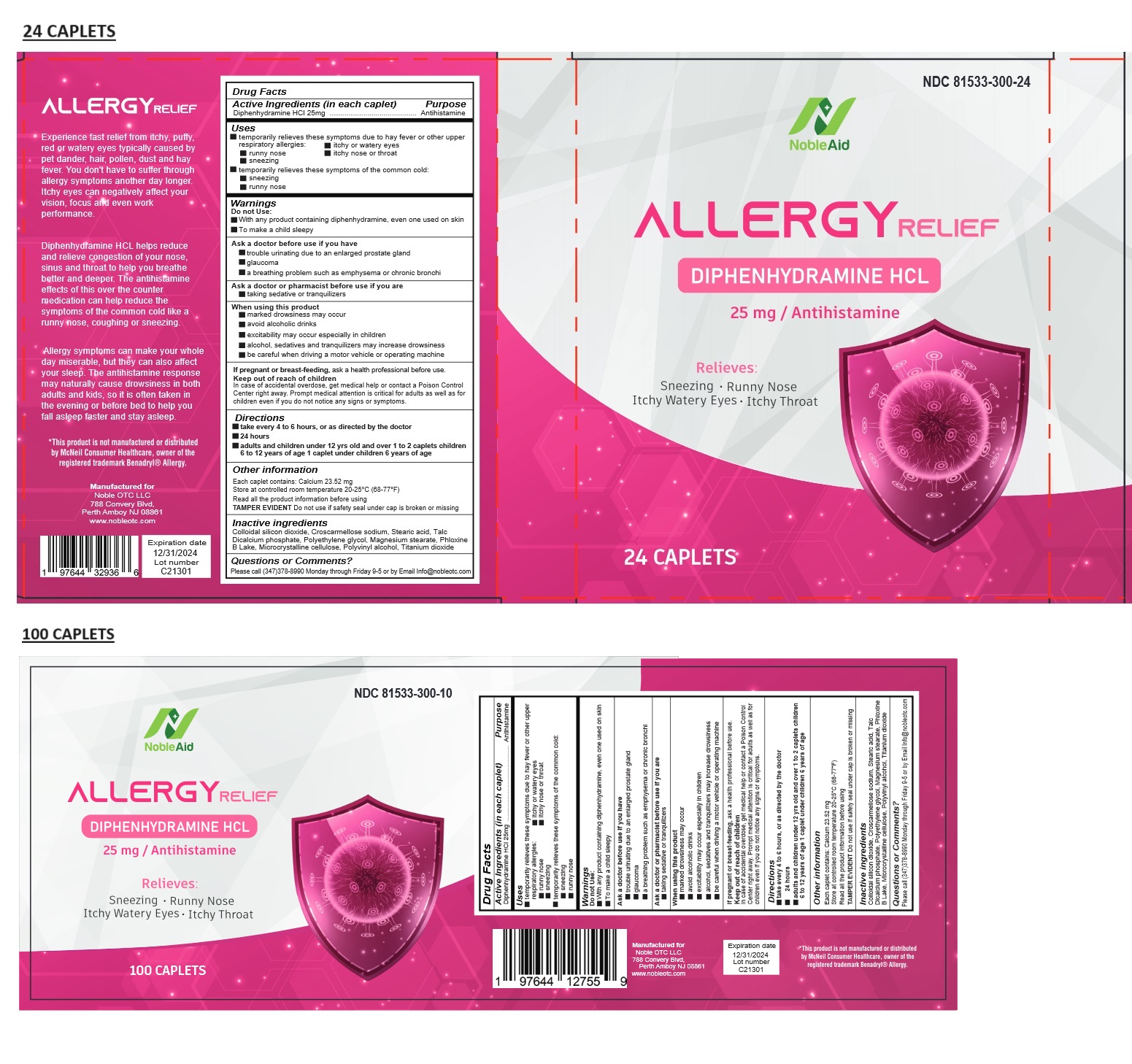 DRUG LABEL: NobleAid ALLERGY RELIEF
NDC: 81533-300 | Form: TABLET
Manufacturer: Noble OTC LLC
Category: otc | Type: HUMAN OTC DRUG LABEL
Date: 20240701

ACTIVE INGREDIENTS: DIPHENHYDRAMINE HYDROCHLORIDE 25 mg/1 1
INACTIVE INGREDIENTS: SILICON DIOXIDE; CROSCARMELLOSE SODIUM; STEARIC ACID; TALC; ANHYDROUS DIBASIC CALCIUM PHOSPHATE; POLYETHYLENE GLYCOL, UNSPECIFIED; MAGNESIUM STEARATE; D&C RED NO. 27; MICROCRYSTALLINE CELLULOSE; POLYVINYL ALCOHOL, UNSPECIFIED; TITANIUM DIOXIDE

NobleAid ALLERGY RELIEF

Active Ingredients (in each caplet)

Diphenhydramine HCl 25mg

Purpose

Antihistamine

Uses

• temporarily relieves these symptoms due to hay fever or other upper respiratory allergies: • itchy or watery eyes
• runny nose • itchy nose or throat
• sneezing

• temporarily relieves these symptoms of the common cold:
• sneezing
• runny nose

Warnings

Do not Use:

• With any product containing diphenhydramine, even one used on skin
• To make a child sleepy

Ask a doctor before use if you have

• trouble urinating due to an enlarged prostate gland
• glaucoma
• a breathing problem such as emphysema or chronic bronchi

Ask a doctor or pharmacist before use if you are
• taking sedative or tranquilizers

When using this product
• marked drowsiness may occur
• avoid alcoholic drinks
• excitability may occur especially in children
• alcohol, sedatives and tranquilizers may increase drowsiness
• be careful when driving a motor vehicle or operating machine

If pregnant or breast-feeding, ask a health professional before use.

KEEP OUT OF REACH OF CHILDREN

In case of accidental overdose, get medical help or contact a Poison Control Center right away. Prompt medical attention is critical for adults as well as for children even if you do not notice any signs or symptoms.

Directions

• take every 4 to 6 hours, or as directed by the doctor
• 24 hours
• adults and children under 12 yrs old and over 1 to 2 caplets children 6 to 12 years of age 1 caplet under children 6 years of age

Other information

Each caplet contains: Calcium 23.52 mg
Store at controlled room temperature 20-25°C (68-77°F)
Read all the product information before using
TAMPER EVIDENT Do not use if safety seal under cap is broken or missing

Inactive ingredients

Colloidal silicon dioxide, Croscarmellose sodium, Stearic acid, Talc, Dicalcium phosphate, Polyethylene glycol, Magnesium stearate, Phloxine B Lake, Microcrystalline cellulose, Polyvinyl alcohol, Titanium dioxide

Questions or Comments?

Please call (347)378-8990 Monday through Friday 9-5 or by Email Info@nobleotc.com

Experience fast relief from itchy, puffy, red or watery eyes typically caused by pet dander, hair, pollen, dust and hay fever. You don't have to suffer through allergy symptoms another day longer. Itchy eyes can negatively affect your vision, focus and even work performance.

Diphenhydramine HCL helps reduce and relieve congestion of your nose, sinus and throat to help you breathe better and deeper. The antihistamine effects of this over the counter medication can help reduce the symptoms of the common cold like a runny nose, coughing or sneezing.

Allergy symptoms can make your whole day miserable, but they can also affect your sleep. The antihistamine response may naturally cause drowsiness in both adults and kids, so it is often taken in the evening or before bed to help you fall asleep faster and stay asleep

*This product is not manufactured or distributed by McNeil Consumer Healthcare, owner of the registered trademark Benadryl® Allergy.

Manufactured for
Noble OTC LLC
788 Convery Blvd,
Perth Amboy NJ 08861
www.nobleotc.com